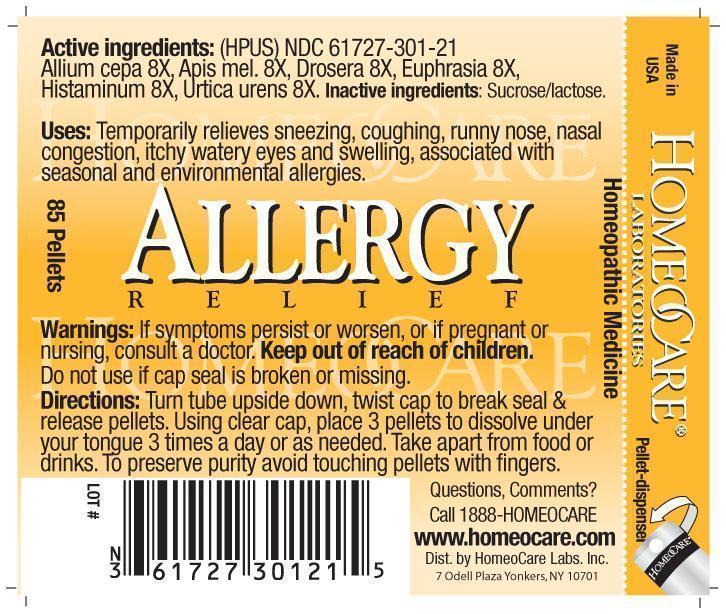 DRUG LABEL: Allergy Relief
NDC: 61727-301 | Form: PELLET
Manufacturer: Homeocare Laboratories
Category: homeopathic | Type: HUMAN OTC DRUG LABEL
Date: 20260112

ACTIVE INGREDIENTS: ONION 8 [hp_X]/4 g; APIS MELLIFERA 8 [hp_X]/4 g; DROSERA ROTUNDIFOLIA 8 [hp_X]/4 g; EUPHRASIA STRICTA 8 [hp_X]/4 g; URTICA URENS 8 [hp_X]/4 g
INACTIVE INGREDIENTS: SUCROSE; LACTOSE

Allergy Relief

Active Ingredients:

Allium Cepa 8X, Apis Mel 8X, Drosera 8X, Euphrasia 8X, Histanium 8X, Urtica Urens 8X.

Inactive Ingredients:

Sucrose/lactose.

Purpose:

Temporarily relieves sneezing, coughing, runny nose, nasal congestion, itchy watery eyes and swelling.

Keep out of reach of children.

Indications & Usage:

Turn tube upside down, twist cap to break seal & release pellets. Using clear cap, place 3 pellets to

Warnings:

If symptoms persist or worsen, or if pregnant or nursing, consult a doctor. Keep out of reach of children. Do not use if cap seal is broken or missing.

Dosage & Administration:

Turn tube upside down, twist cap to break seal & release pellets. Using clear cap, place 3 pellets to dissolve under your tongue 3 times a day or as needed.

Allergy Relief

Homeopathic Medicine

85 Pellets

allergy relief